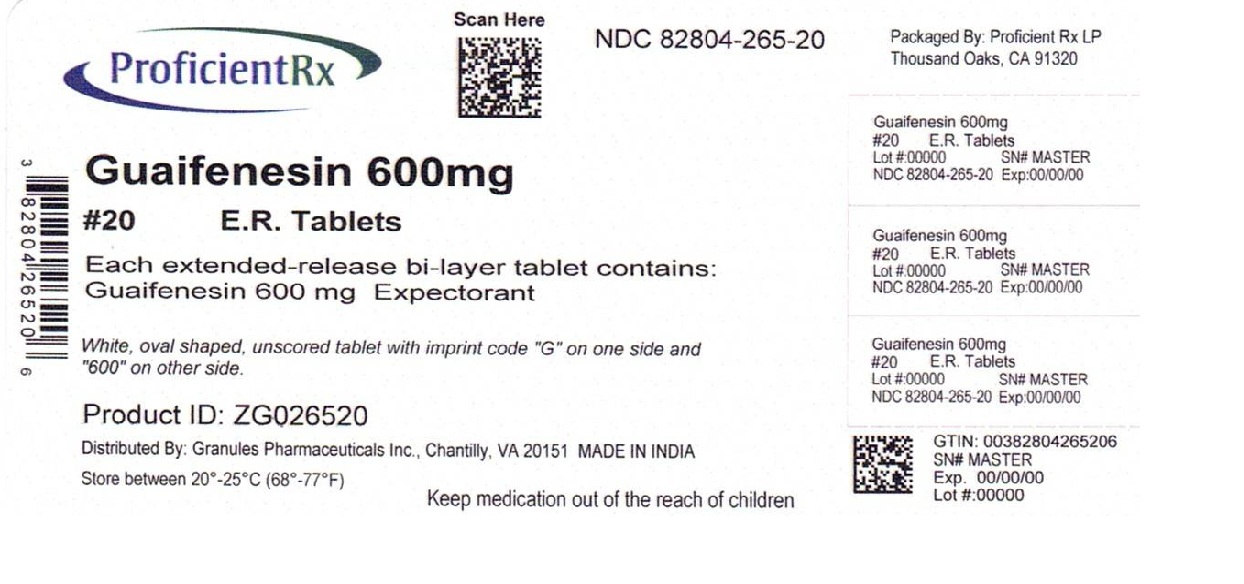 DRUG LABEL: GUAIFENESIN
NDC: 82804-265 | Form: TABLET, EXTENDED RELEASE
Manufacturer: Proficient Rx LP
Category: otc | Type: HUMAN OTC DRUG LABEL
Date: 20260201

ACTIVE INGREDIENTS: GUAIFENESIN 600 mg/1 1
INACTIVE INGREDIENTS: SODIUM STARCH GLYCOLATE TYPE A POTATO; MAGNESIUM STEARATE; CARBOMER HOMOPOLYMER TYPE B (ALLYL SUCROSE CROSSLINKED); MICROCRYSTALLINE CELLULOSE; HYPROMELLOSE 2910 (5 MPA.S); HYPROMELLOSE 2910 (10000 MPA.S)

Guaifenesin Extended-Release Tablets 600mg

ACTIVE INGREDIENT(S)

Guaifenesin 600 mg (for 600mg)

PURPOSE

Expectorant

USE(S)

- helps loosen phlegm (mucus) and thin bronchial secretions to rid the bronchial passageways of bothersome mucus and make coughs more productive

WARNINGS

Do not use

- for children under 12 years of age

ASK A DOCTOR BEFORE USE IF YOU HAVE

- persistent or chronic cough such as occurs with smoking, asthma, chronic bronchitis, or emphysema
- cough accompanied by too much phlegm (mucus)

STOP USE AND ASK DOCTOR IF

- cough lasts more than 7 days, comes back, or occurs with fever, rash, or persistent headache. These could be signs of a serious illness.

If pregnant or breast-feeding,

ask a health professional before use.

KEEP OUT OF REACH OF CHILDREN

In case of overdose, get medical help or contact a Poison Control Center right away
(1-800-222-1222)

DIRECTIONS

- do not crush, chew, or break tablet
- take with a full glass of water
- this product can be administered without regard for timing of meals
- adults and children 12 years of age and over: 1 or 2 tablets every 12 hours. Do not exceed 4 tablets in 24 hours(For 600mg)
- children under 12 years of age: do not use

OTHER INFORMATION

- do not use if foil inner seal is broken or missing.
- store between 20-25°C (68-77°F)

INACTIVE INGREDIENTS

carbomer homopolymer type B; hypromellos, magnesium stearate, microcrystalline cellulose, sodium starch glycolate

QUESTIONS OR COMMENTS

Contact 1-877-770-3183
Mon-Fri 8:00 AM EST to 5:00 PM PST.
All trademarks are property of their respective owners.MUCINEX is the registered trademark of Reckitt Benckiser LLC.